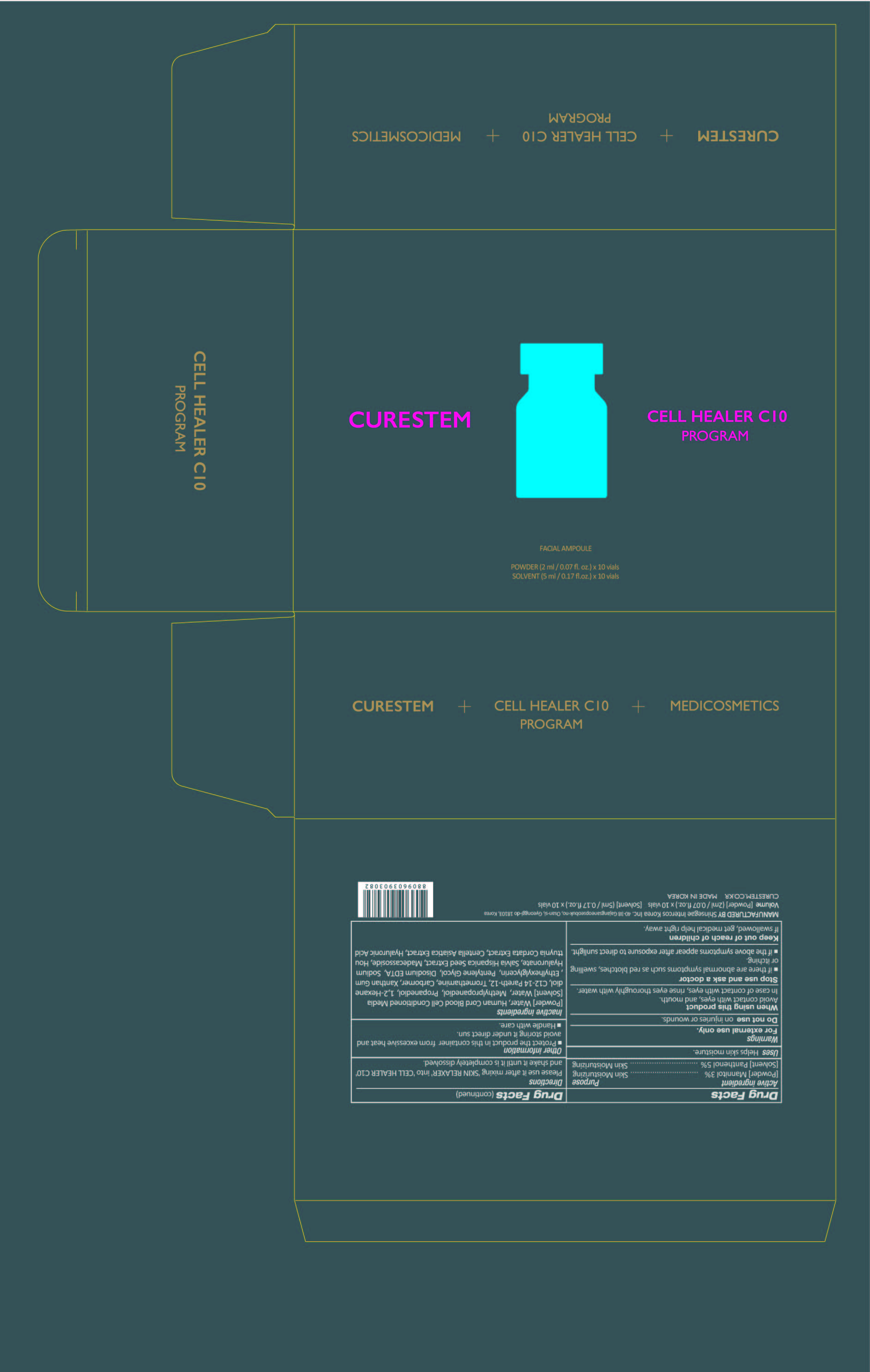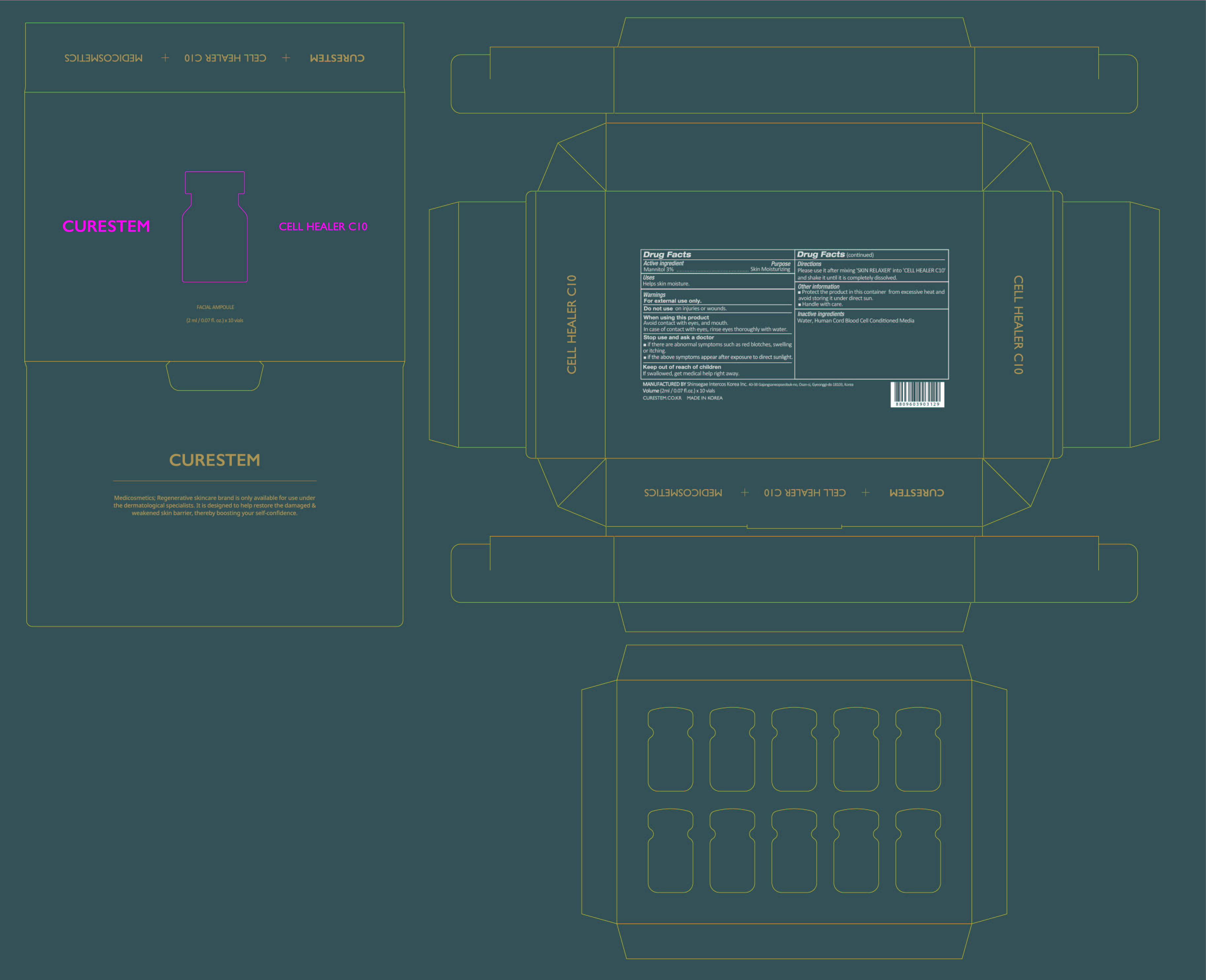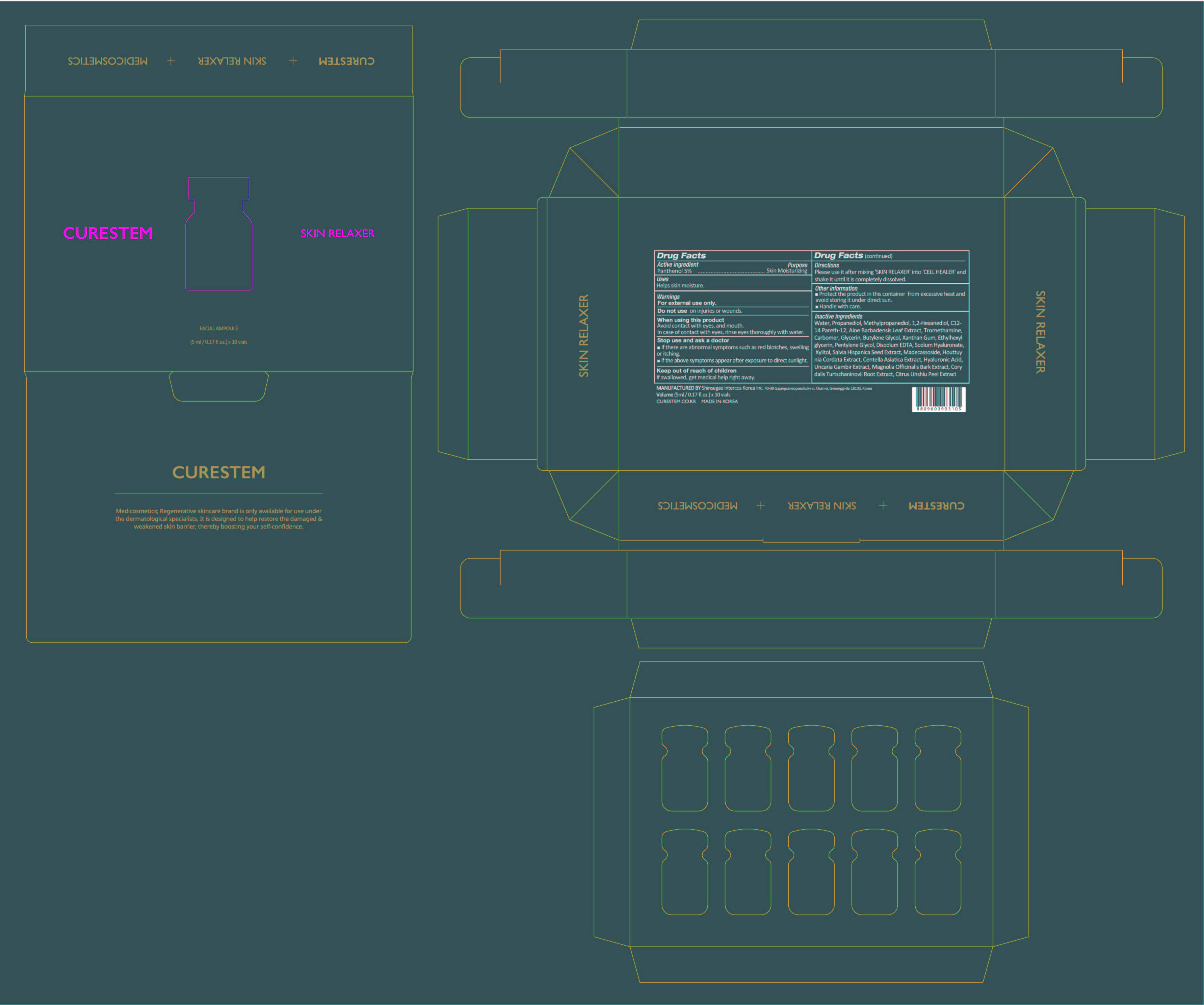 DRUG LABEL: CURESTEM CELL HEALER C10 PROGRAM
NDC: 78521-600 | Form: KIT | Route: TOPICAL
Manufacturer: DNK CORPORATION LTD.
Category: otc | Type: HUMAN OTC DRUG LABEL
Date: 20200608

ACTIVE INGREDIENTS: MANNITOL 0.06 g/2 mL; PANTHENOL 0.25 g/5 mL
INACTIVE INGREDIENTS: WATER; CORD BLOOD; METHYLPROPANEDIOL; XANTHAN GUM; ETHYLHEXYLGLYCERIN; HYALURONATE SODIUM; SALVIA HISPANICA SEED; CENTELLA ASIATICA; HYALURONIC ACID; TROMETHAMINE; CARBOMER HOMOPOLYMER, UNSPECIFIED TYPE; PENTYLENE GLYCOL; WATER; EDETATE DISODIUM; MADECASSOSIDE; PROPANEDIOL; 1,2-HEXANEDIOL; C12-14 PARETH-12; HOUTTUYNIA CORDATA FLOWERING TOP; GLYCERIN; BUTYLENE GLYCOL; CORYDALIS TURTSCHANINOVII WHOLE; XYLITOL; ALOE VERA LEAF; UNCARIA GAMBIR WHOLE; MAGNOLIA OBOVATA BARK; TANGERINE PEEL

CURESTEM CELL HEALER C10 PROGRAM : 78521-600-20

Active ingredients

[Powder] Mannitol 3%

[Solvent] Panthenol 5%

Purpose

[Powder] Mannitol 3% Skin Moisturizing

[Solvent] Panthenol 5% Skin Moisturizing

Uses

Helps skin moisture.

Warnings

For external use only.

Do not use

on injuries or wounds.

When using this product

Avoid contact with eyes, and mouth. In case of contact with eyes, rinse eyes thoroughly with water.

Stop use and ask a doctor

■ if there are abnormal symptoms such as red blotches, swelling or itching.

■ if the above symptoms appear after exposure to direct sunlight.

Keep out of reach of children

If swallowed, get medical help or contact a Poison Control Center right away.

Directions

Please use it after mixing 'SKIN RELAXER' into 'CELL HEALER C10'

and shake it until it is completely dissolved.

Other information

■ Protect the product in this container from excessive heat and

avoid storing it under direct sun.

■ Handle with care.

Inactive ingredients

[Powder] Water, Human Cord Blood Cell Conditioned Media

[Solvent] Water, Propanediol, Methylpropanediol, 1,2-Hexanediol,

C12-14 Pareth-12, Aloe Barbadensis Leaf Extract, Tromethamine,

Carbomer, Glycerin, Butylene Glycol, Xanthan Gum, Ethylhexylglycerin,

Pentylene Glycol, Disodium EDTA, Sodium Hyaluronate,

Xylitol, Salvia Hispanica Seed Extract, Madecassoside, Houttuynia Cordata Extract,

Centella Asiatica Extract, Hyaluronic Acid, Uncaria Gambir Extract,

Magnolia Officinalis Bark Extract, Corydalis Turtschaninovii Root Extract, Citrus Unshiu Peel Extract